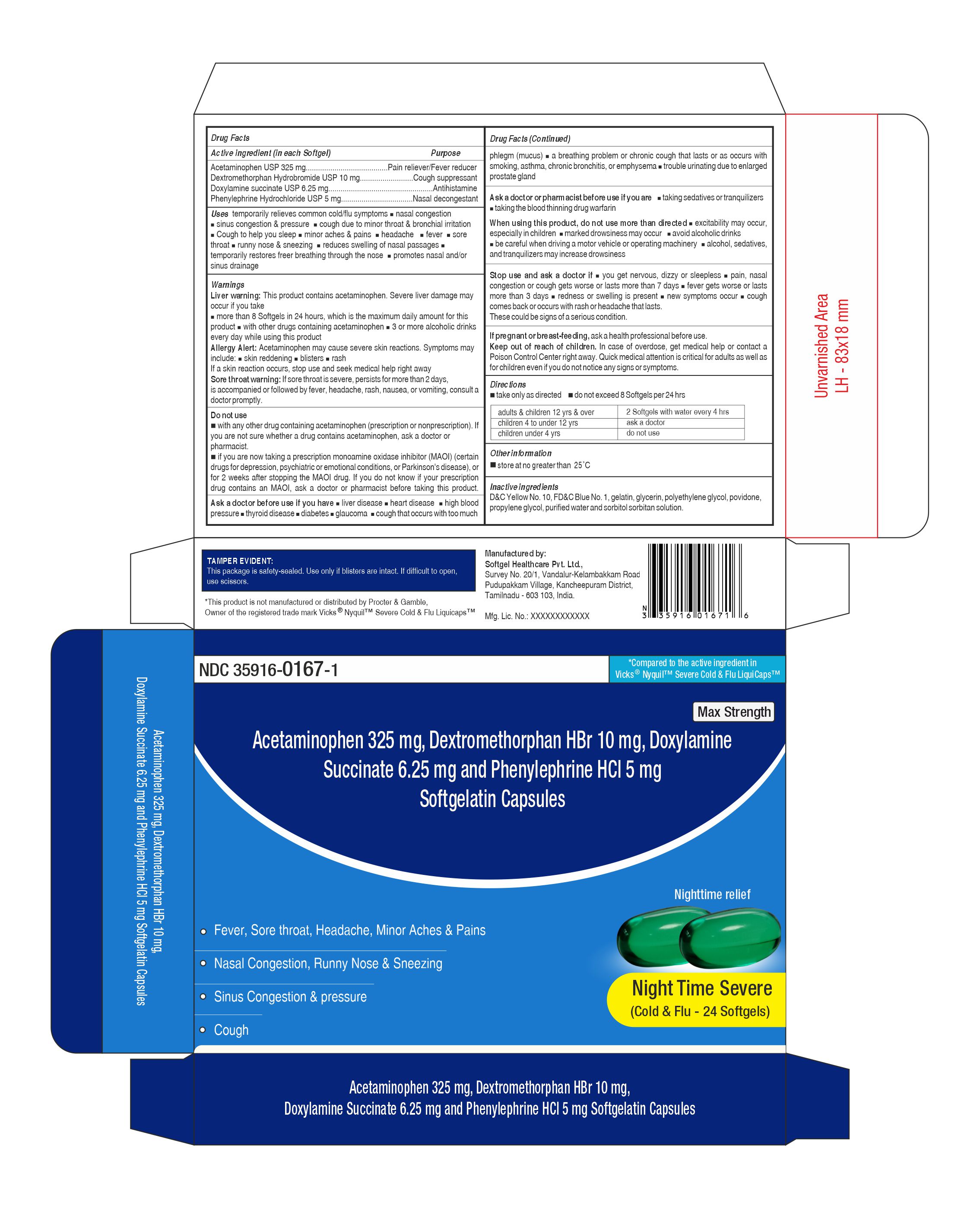 DRUG LABEL: Acetaminophen, Dextromethorphan Hydrobromide, Doxylamine Succinate and Phenylephrine Hydrochloride
NDC: 35916-0167 | Form: CAPSULE, LIQUID FILLED
Manufacturer: SOFTGEL HEALTHCARE PRIVATE LIMITED
Category: otc | Type: HUMAN OTC DRUG LABEL
Date: 20260128

ACTIVE INGREDIENTS: ACETAMINOPHEN 325 mg/1 1; DEXTROMETHORPHAN HYDROBROMIDE 10 mg/1 1; PHENYLEPHRINE HYDROCHLORIDE 5 mg/1 1; DOXYLAMINE SUCCINATE 6.25 mg/1 1
INACTIVE INGREDIENTS: D&C YELLOW NO. 10; GLYCERIN; PROPYLENE GLYCOL; GELATIN; WATER; FD&C BLUE NO. 1; POLYETHYLENE GLYCOL, UNSPECIFIED; POVIDONE; SORBITOL

Acetaminophen 325 mg , Dextromethorphan Hydrobromide 10 mg, Doxylamine Succinate 6.25 mg and Phenylephrine Hydrochloride 5 mg (Night Time Severe)

Active ingredients (in each Softgel)

Acetaminophen USP 325 mg

Dextromethorphan Hydrobromide USP 10 mg

Doxylamine succinate USP 6.25 mg

Phenylephrine Hydrochloride USP 5 mg

Purpose

Pain reliever/Fever reducer

Cough suppressant

Antihistamine

Nasal decongestant

Uses

temporarily relieves common cold/flu symptoms:

- nasal congestion
- sinus congestion & pressure
- cough due to minor throat & bronchial irritation
- Cough to help you sleep
- minor aches & pains
- headache
- fever
- sore throat
- runny nose & sneezing
- reduces swelling of nasal passages
- temporarily restores free breathing through the nose
- promotes nasal and/or sinus drainage

Warnings

Liver warning:

This product contains acetaminophen. Severe liver damage may occur if you take

- more than 8 Softgels in 24 hrs, which is the maximum daily amount for this product
- with other drugs containing acetaminophen
- 3 or more alcoholic drinks every day while using this product

Allergy Alert:

Acetaminophen may cause severe skin reactions. Symptoms may include:

- Skin reddening
- Blisters
- Rash

If a skin reaction occurs, stop use and seek medical help right away

Sore throat warning:

If sore throat is severe, persists for more than 2 days, is accompanied or followed by fever, headache, rash, nausea, or vomiting, consult a doctor promptly.

Do not use

- with any other drug containing acetaminophen (prescription or nonprescription). If you are not sure whether a drug contains acetaminophen, ask a doctor or pharmacist.
- if you are now taking a prescription monoamine oxidase inhibitor (MAOI) (certain drugs for depression, psychiatric or emotional conditions, or Parkinson's disease), or for 2 weeks after stopping the MAOI drug. If you do not know if your prescription drug contains an MAOI, ask a doctor or pharmacist before taking this product.

Ask a doctor before use if you have

- liver disease
- heart disease
- high blood pressure
- thyroid disease
- diabetes
- glaucoma
- cough that occurs with too much phlegm (mucus)
- a breathing problem or chronic cough that lasts or as occurs with smoking, asthma,chronic bronchitis, or emphysema
- trouble urinating due to enlarged prostate gland

Ask a doctor or pharmacist before use if you are

- taking sedatives or tranquilizers
- taking the blood thinning drug warfarin

When using this product

- do not use more than directed
- excitability may occur, especially in children
- marked drowsiness may occur
- avoid alcoholic drinks
- be careful when driving a motor vehicle or operating machinery
- alcohol, sedatives, & tranquilizers may increase drowsiness

Stop use and ask a doctor if

- you get nervous, dizzy or sleepless
- pain, nasal congestion, or cough gets worse or lasts more than 7 days
- fever gets worse or lasts more than 3 days
- redness or swelling is present
- new symptoms occur
- cough comes back or occurs with rash or headache that lasts.

These could be signs of a serious condition.

If pregnant or breast-feeding,

ask a health professional before use.

Keep out of reach of children.

Overdosage

In case of overdose, get medical help or contact a Poison Control Center right away.Quick medical attention is critical for adults as well as for children even if you do not notice any signs or symptoms.

Directions

- take only as directed
- do not exceed 8 Softgels per 24 hrs
  Adults & children 12 years & over | 2 softgels with water every 4 hours
  Children 4 to under 12 years | Ask a doctor
  Children under 4 years | Do not use

Other information

Store at no greater than 25ºC

Inactive ingredients

FD&C Blue No.1, D&C Yellow No.10, gelatin, glycerin, polyethylene glycol, povidone, propylene glycol, purified water and sorbitol sorbitan solution.

TAMPER EVIDENT

This package is safety-sealed. Use only if blisters are intact. If difficult to open, use scissors.

Manufactured by

Softgel Healthcare Pvt. Ltd.,
Survey No. 20/1, Vandalur-Kelambakkam Road,
Pudupakkam Village, Kancheepuram District,
Tamilnadu - 603 103, India.
Mfg. Lic. No.: XXXXXXXXXXXX